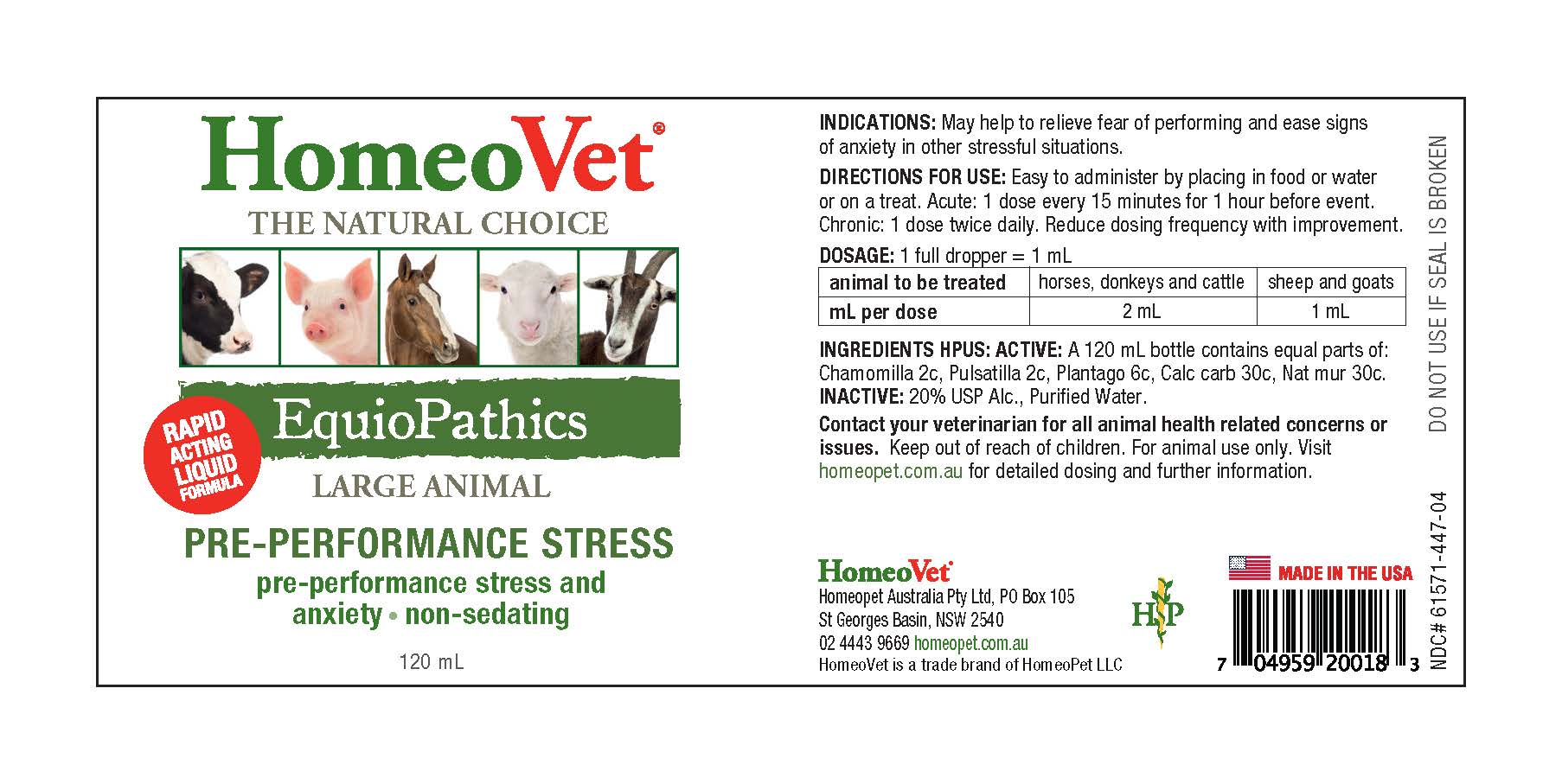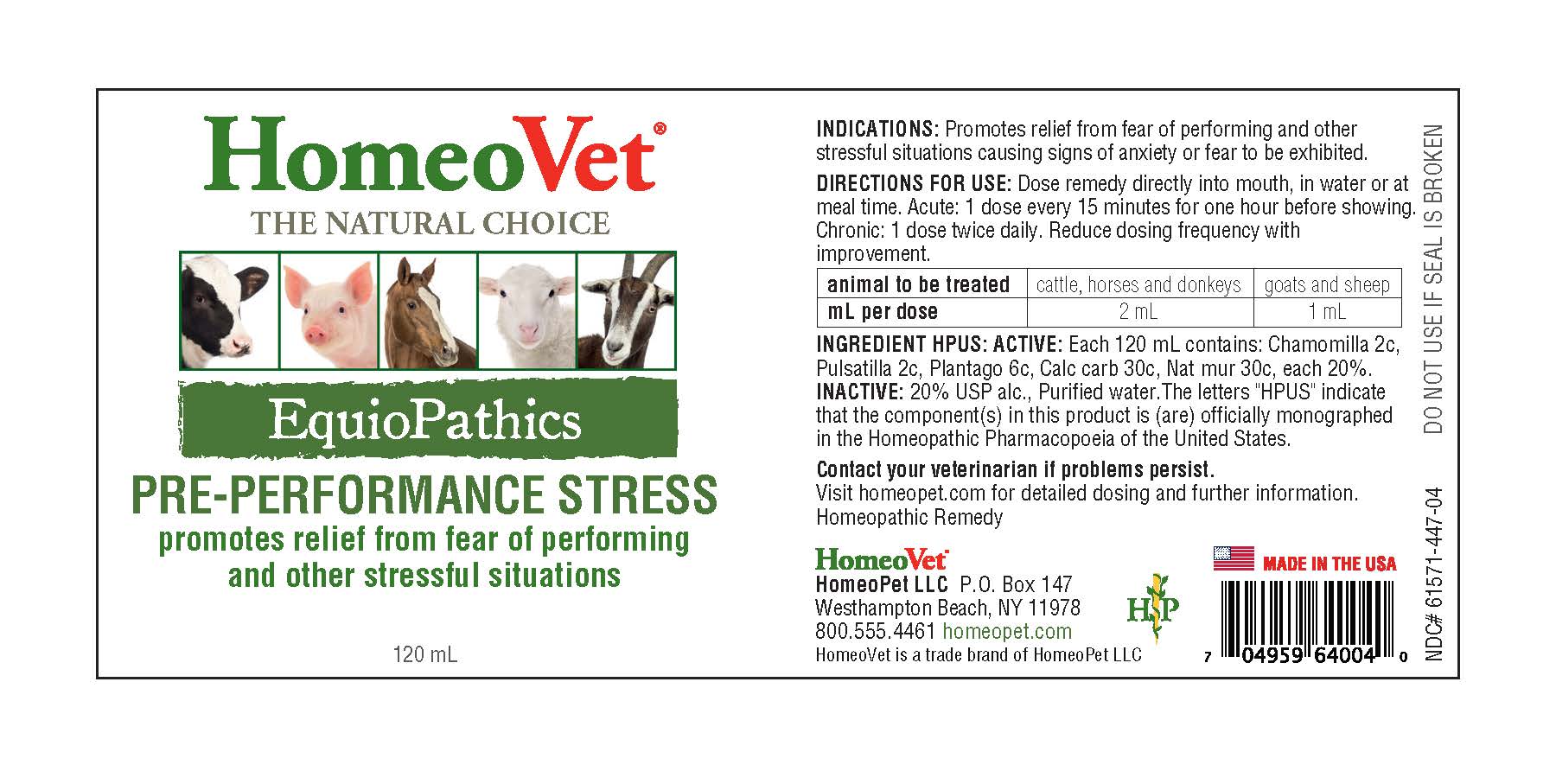 DRUG LABEL: EquioPathics Pre-Performance Stress
NDC: 61571-447 | Form: LIQUID
Manufacturer: HomeoPet, LLC
Category: homeopathic | Type: OTC ANIMAL DRUG LABEL
Date: 20251211

ACTIVE INGREDIENTS: SODIUM CHLORIDE 30 [hp_C]/120 mL; CHAMOMILE 2 [hp_C]/120 mL; PULSATILLA PATENS 2 [hp_C]/120 mL; OYSTER SHELL CALCIUM CARBONATE, CRUDE 30 [hp_C]/120 mL; PLANTAGO MAJOR 6 [hp_C]/120 mL
INACTIVE INGREDIENTS: ALCOHOL; WATER

EquioPathics Pre-Performance Stress

INDICATIONS

Promotes relief from fear of performing and other stressful situations causing signs of anxiety or fear to be exhibited.

EquioPathics Pre-Performance Stress

Promotes relief from fear of performing and other stressful situations

DIRECTIONS FOR USE AND DOSAGE

Dose remedy direclty into mouth, in water or at meal time. Acute: 1 dose every 15 minutes for one hour before showing. Chronic 1 dose twice daily. Reduce dosing frequency with improvement.

animal to be treated | cattle, horses and donkeys | goats and sheep
mL per dose | 2 mL | 1 mL

Ingredients HPUS: ACTIVE

Chamomilla 2c, Pulsatilla 2c, Plantago 6c, Calc carb 30c, Nat mur 30c

Inactive Ingredients

USP Alcohol, Purified Water

ASK DOCTOR

Contact your veterinarian if problems persist.

Visit homeopet.com for detailed dosing and further information.

Homeopathic Remedy